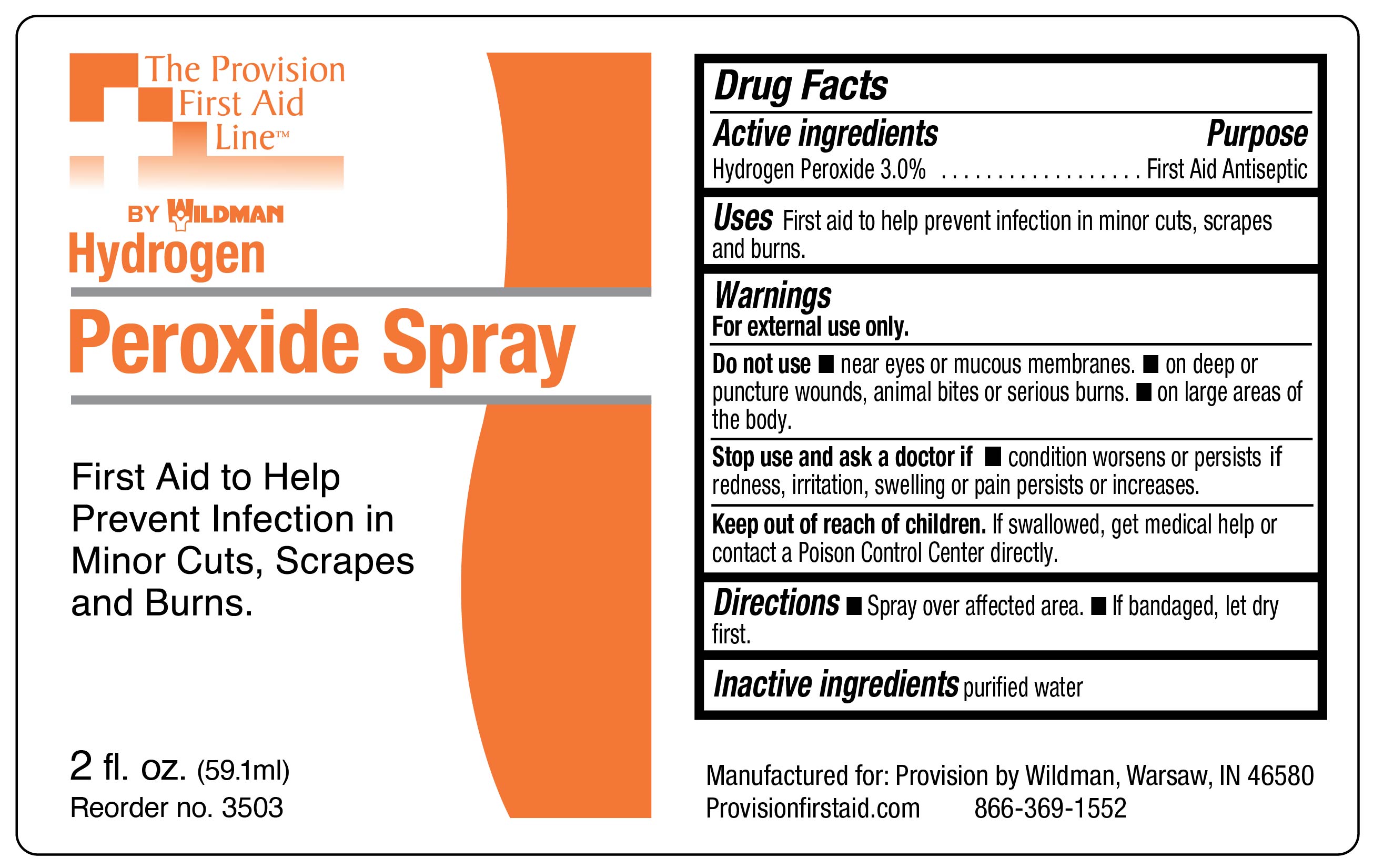 DRUG LABEL: Hydrogen Peroxide
NDC: 84269-3503 | Form: SPRAY
Manufacturer: Wildman Business Group
Category: otc | Type: HUMAN OTC DRUG LABEL
Date: 20240601

ACTIVE INGREDIENTS: HYDROGEN PEROXIDE 30 mg/1 mL
INACTIVE INGREDIENTS: WATER

Hydrogen Peroxide spray

Drug Facts

Active Ingredients

Hydrogen Peroxide 3.0%

Purpose

First Aid Antiseptic

Uses

First aid to help prevent infection in minor cuts, scrapes and burns

Warnings

For external use only.

Do not use

- near eyes or mucous membranes
- on deep or puncture wounds, animal bites, or serious burns

Keep out of reach of children.

Caution

- not for use on large areas of the body
- if redness, irritation, swelling or pain persists or increases, discontinue use and consult a physician

Directions

- spray over affected area
- if bandaged, let dry first

Inactive ingredients

purified water

PRINCIPAL DISPLAY PANEL – 2 oz. bottle label

Provision by Wildman

Hydrogen
Peroxide Spray

First Aid to Help
Prevent Infection in
Minor Cuts, Scrapes
and Burns.

2 fl. oz. (59.1ml)
Reorder no. 3503